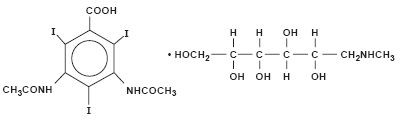 DRUG LABEL: Unknown
Manufacturer: Amersham Health Inc.
Category: prescription | Type: HUMAN PRESCRIPTION DRUG LABELING
Date: 20070803

HYPAQUE™ Meglumine
(Diatrizoate Meglumine Injection, USP)
60%

Sterile Aqueous Injection

For Excretory Urography
Cerebral Angiography
Peripheral Arteriography
Venography
Direct Cholangiography
Splenoportography
Arthrography
Discography
Contrast Enhancement of Computed Tomographic Head Imaging

NOT FOR INTRATHECAL USE

Rx ONLY

DESCRIPTION

HYPAQUE meglumine, brand of diatrizoate meglumine, is a water-soluble, radiopaque diagnostic medium. It is a triiodinated benzoic acid derivative containing 47.06 percent organically bound iodine. It is constituted as an iodinated anion (diatrizoate) and a radiolucent cation (meglumine).

HYPAQUE meglumine 60 percent (w/v) is a sterile aqueous solution containing 60 g of the meglumine salt of diatrizoic acid per 100 mL of solution. The solution is a clear-colorless to pale yellow liquid, and the pH is adjusted between 6.5 and 7.7 with diatrizoic acid or meglumine solution. It is a relatively thermostable solution and may be autoclaved without harmful effects, although it should be protected from strong light. The 60 percent solution contains edetate calcium disodium 1:10,000 as a sequestering stabilizing agent. Each 1 mL contains approximately 282 mg of organically bound iodine. The viscosity of the solution is 6.17 cp at 25°C and 4.12 cp at 37°C.

It is hypertonic to blood with an osmolality of 1415 mosm/kg (determined by VPO). A 13 percent solution (w/v) is isotonic.

It is a colorless, microcrystalline solid which is readily soluble in water.

It is meglumine 3,5-diacetamido-2,4,6-triiodobenzoate (C11H9I3N2O4 • C7H17NO5) with a molecular weight of 809.13, and has the following structural formula:

CLINICAL PHARMACOLOGY

Intravascular injection of a radiopaque diagnostic agent opacifies those vessels in the path of the flow of the contrast medium, permitting radiographic visualization of the internal structures of the human body until significant hemodilution occurs.

At physiologic pH, the water soluble contrast media are completely dissociated into a radiopaque anion and a solubilizing cation. While circulating in tissue fluids, the compound remains ionized. However, it is not metabolized but excreted unchanged in the urine, each diatrizoate molecule remaining "obligated" to its meglumine moiety.

Following intravenous injection, the radiopaque diagnostic agents are immediately diluted in the circulating plasma. Equilibrium is reached with the extracellular compartment at about 10 minutes. Hence, the plasma concentration at 10 minutes is closely related to the dose corrected to body size.

The pharmacokinetics of the intravenously administered radiopaque contrast media are usually best described by a two compartment model with a rapid alpha phase for drug distribution and a slow beta phase for drug elimination. In patients with normal renal function, the alpha and beta half-lives were respectively 30 minutes and 120 minutes for diatrizoate. But in patients with renal functional impairment, the elimination half-life for the beta phase can be prolonged up to several days.

Injectable radiopaque diagnostic agents are excreted either through the liver or through the kidneys. The two excretory pathways are not mutually exclusive, but the main route of excretion seems to be governed by the affinity of the contrast medium for serum albumin. From 0% to 10% of diatrizoate sodium is bound to serum protein.

Diatrizoate salts are excreted unchanged predominantly through the kidneys by glomerular filtration. The amount excreted by the kidney during any period of time is determined by the filtered load; ie, the product of plasma contrast media concentration and glomerular filtration rate. The plasma concentration is dependent upon the dose administered and the body size. The glomerular filtration rate varies with the body size, sex, age, circulatory dynamics, diuretic effect of the drug, and renal function. In patients with normal renal function the maximum urinary concentration of diatrizoate meglumine occurs within 10 minutes with 12 percent of the administered dose being excreted. The mean values of cumulative urinary excretion for diatrizoate meglumine expressed as percentage of administered dose are 38 percent at 60 minutes, 45 percent at 3 hours, and 94 to 100 percent at 24 hours.

Urinary excretion of contrast media is delayed in infants younger than 1 month and in patients with urinary tract obstruction. The urinary iodine concentration is higher with the sodium salt of diatrizoic acid than with the meglumine salt.

The liver and small intestine provide the major alternate route of excretion for diatrizoate. In patients free of severe renal disease, the fecal recovery is less than 2 percent of the administered dose. In patients with severe renal impairment the excretion of these contrast media through the gallbladder and into the small intestine sharply increases; up to 20 percent of the administered dose has been recovered in the feces in 48 hours.

Saliva is a minor secretory pathway for injectable radiopaque diagnostic agents. In patients with normal renal function, minimal amounts of contrast media are secreted unchanged. However, in uremic patients small amounts of free iodides resulting from deiodination prior to administration or in vivo, have been detected in the saliva.

Diatrizoate salts cross the placental barrier in humans by simple diffusion and appear to enter fetal tissue passively. No apparent harm to the fetus was observed when diatrizoate sodium and diatrizoate meglumine were injected intravenously 24 hours prior to delivery. However, abnormal neonatal opacification of the small intestine and colon were detected 4 to 6 days after delivery. Procedures including radiation involve a certain risk related to the exposure of the fetus. (See PRECAUTIONS—General, Pregnancy Category C.)

Injectable radiopaque diagnostic agents are excreted unchanged in human milk. (See PRECAUTIONS-General, Nursing Mothers.)

Computerized Tomography

HYPAQUE meglumine 60 percent can be administered as an intravenous bolus for brain tissue enhancement using computerized tomography. Increased tissue contrast differential for the scan is achieved either because of increased vascular (arterial, venous, or capillary bed) contrast or by blood brain barrier penetration of the medium (or its absence) in certain localized areas of disrupted vascular permeability. The degree of tissue enhancement caused by increased blood contrast is directly related to blood iodine content. However, the degree of enhancement due to extravascular accumulation of iodine resulting from blood brain barrier disruption will depend on the extent of disruption, the blood level of iodine, and the time delay prior to scanning. The nature of the pathology will determine whether an immediate or delayed scan is optimal.

Effects of Steroid Therapy

The anti-inflammatory and antiedema effects in patients receiving steroid therapy have interfered with the expected distribution of CT tissue enhancement on the scan in certain diseases.

INDICATIONS AND USAGE

HYPAQUE meglumine 60 percent is indicated for excretory urography; cerebral angiography; peripheral arteriography; venography; operative, T-tube, or percutaneous transhepatic cholangiography; splenoportography; arthrography; discography; and contrast enhancement of computed tomographic head imaging.

Urography

Diatrizoate salts are used in small, medium, and large dose urography (see Dosage and Administration-EXCRETORY UROGRAPHY). Visualization of the urinary tract can be achieved by either direct intravenous bolus injection, intravenous drip infusion, or incidentally following intra-arterial procedures. Visualization of the urinary tract is delayed in infants less than 1 month old, and in patients with urinary tract obstruction (see CLINICAL PHARMACOLOGY).

Contrast Enhancement of Computed Tomographic Head Imaging

Injectable radiopaque contrast media may be used to refine diagnostic precision in areas of the brain which may not otherwise have been satisfactorily visualized.

Tumors

Radiopaque diagnostic agents may be useful to investigate the presence and extent of certain malignancies such as: gliomas including malignant gliomas, glioblastomas, astrocytomas, oligodendrogliomas and gangliomas, ependymomas, medulloblastomas, meningiomas, neuromas, pinealomas, pituitary adenomas, craniopharyngiomas, germinomas, and metastatic lesions.

The usefulness of contrast enhancement for the investigation of the retrobulbar space and in cases of low grade or infiltrative glioma has not been demonstrated.

In calcified lesions, there is less likelihood of enhancement. Following therapy, tumors may show decreased or no enhancement.

The opacification of the inferior vermis following contrast media administration has resulted in false-positive diagnosis in a number of normal studies.

Nonneoplastic Conditions

The use of injectable radiopaque diagnostic agents may be beneficial in the image enhancement of nonneoplastic lesions. Cerebral infarctions of recent onset may be better visualized with contrast enhancement, while some infarctions are obscured if contrast media are used. The use of iodinated contrast media results in contrast enhancement in about 60 percent of cerebral infarctions studied from one to four weeks from the onset of symptoms.

Sites of active infection may also be enhanced following contrast media administration.

Arteriovenous malformations and aneurysms will show contrast enhancement. For these vascular lesions, the enhancement is probably dependent on the iodine content of the circulating blood pool.

Hematomas and intraparenchymal bleeders seldom demonstrate any contrast enhancement. However, in cases of intraparenchymal clot, for which there is no obvious clinical explanation, contrast media administration may be helpful in ruling out the possibility of associated arteriovenous malformation.

Angiography

Diatrizoate salts are used for radiographic studies throughout the cardiovascular system.

Intravascular radiopaque diagnostic agents of high concentration are not recommended for cerebral or spinal angiography (see CONTRAINDICATIONS—General), and contrast agents with the lowest compatible viscosity and higher concentration of iodine (310 mg/mL to 480 mg/mL of bound iodine) must be used for angiocardiography. Contrast media approaching serum ionic content and osmolality have less potential for deleterious effects on the myocardium (see PRECAUTIONS—General, Drug Interactions).

Addition of chelating agents may contribute to toxicity in coronary angiography, and the sodium content of angiographic agents used in coronary arteriography is of crucial importance.

In addition to the following general CONTRAINDICATIONS, WARNINGS, PRECAUTIONS and ADVERSE REACTIONS, there are additional listings in these categories under the particular procedures.

CONTRAINDICATION—General

HYPAQUE meglumine 60 percent has no absolute contraindications in its recommended uses (see general WARNINGS and PRECAUTIONS).

Do not use HYPAQUE meglumine 60 percent solution for myelography or for examination of dorsal cysts or sinuses which might communicate with the subarachnoid space. Even a small amount in the subarachnoid space may produce convulsions and result in fatality. Epidural injection is also contraindicated.

Urography and large dose vascular procedures are contraindicated in dehydrated azotemic patients. (See also PRECAUTIONS—General.)

WARNINGS—General

SEVERE ADVERSE EVENTS—INADVERTENT INTRATHECAL ADMINISTRATION

Serious adverse reactions have been reported due to the inadvertent intrathecal administration of iodinated contrast media that are not indicated for intrathecal use. These serious adverse reactions include: death, convulsions, cerebral hemorrhage, coma, paralysis, arachnoiditis, acute renal failure, cardiac arrest, seizures, rhabdomyolysis, hyperthermia, and brain edema. Special attention must be given to insure that this drug product is not administered intrathecally.

Ionic iodinated contrast media inhibit blood coagulation, in vitro, more than nonionic contrast media. Nonetheless, it is prudent to avoid prolonged contact of blood with syringes containing ionic contrast media.

Serious, rarely fatal, thromboembolic events causing myocardial infarction and stroke have been reported during angiographic procedures with both ionic and nonionic contrast media. Therefore, meticulous intravascular administration technique is necessary, particularly during angiographic procedures, to minimize thromboembolic events. Numerous factors, including length of procedure, catheter and syringe material, underlying disease state and concomitant medications may contribute to the development of thromboembolic events. For these reasons, meticulous angiographic techniques are recommended including close attention to guidewire and catheter manipulation, use of manifold systems and/or three-way stopcocks, frequent catheter flushing with heparinized saline solutions and minimizing the length of the procedure. The use of plastic syringes in place of glass syringes has been reported to decrease but not eliminate the likelihood of in vitro clotting.

Excretory urography is potentially hazardous in patients with multiple myeloma. In some of those patients, therapeutically resistant anuria resulting in progressive uremia, renal failure and eventually death has followed this procedure. Although neither the contrast agent nor dehydration has been proved separately to be the cause of anuria in myelomatous patients, it has been speculated that the combination of both may be causative. The risk of excretory urography in myelomatous patients is not a contraindication to the procedure; however, they require special precautions. Partial dehydration in the preparation of these patients for the examination is not recommended since this may predispose to the precipitation of myeloma protein in the renal tubules. Myeloma, which occurs most commonly in persons over age 40, should be considered before instituting urographic procedures.

Contrast media may promote sickling in individuals who are homozygous for sickle cell disease when the material is injected intravenously or intra-arterially.

Administration of radiopaque materials to patients known or suspected of having pheochromocytoma should be performed with extreme caution. If, in the opinion of the physician, the possible benefits of such procedures outweigh the considered risks, the procedures may be performed; however, the amount of radiopaque medium injected should be kept to an absolute minimum. The blood pressure should be assessed throughout the procedure and measures for treatment of a hypertensive crisis should be available.

Recent reports of thyroid storm occurring following the intravascular use of iodinated radiopaque diagnostic agents in patients with hyperthyroidism or with an autonomously functioning thyroid nodule suggest that this additional risk be evaluated in such patients before use of HYPAQUE meglumine.

Contrast media administered for cardiac catheterization and angiocardiography may cause cellular injury to circulating lymphocytes. Chromosomal damage in humans includes inhibition of mitosis, increases in the number of micronuclei, and chromosome aberrations. The damages appear to be related to the contrast medium itself rather than to the x-ray radiation. It is to be noted that those agents have not been adequately tested in animal or laboratory systems.

Urography should be performed with caution in patients with severely impaired renal function and patients with combined renal and hepatic disease.

Subcutaneous extravasation, chiefly because of hypertonic cellulitis, causes transitory stinging. If the volume extravasated is small, ill effects are very unlikely. However, if the extravasation is extensive especially in poorly vascularized areas (eg, dorsum of the foot or hand), and especially in the presence of vascular disease, skin slough may occur. Injection of sterile water to dilute or addition of spreading agents to speed absorption have not been successful and may aggravate the condition.

Selective spinal arteriography or arteriography of trunks providing spinal branches can cause mild to severe muscle spasm. However, serious neurologic sequelae, including permanent paralysis, have occasionally been reported. (See also ANGIOGRAPHY, Precaution.)

In patients with subarachnoid hemorrhage, a rare association between contrast administration and clinical deterioration, including convulsions and death, has been reported. Therefore, administration of intravascular iodinated ionic contrast media in these patients should be undertaken with caution.

PRECAUTIONS—General

Diagnostic procedures which involve the use of radiopaque diagnostic agents should be carried out under the direction of personnel with the prerequisite training and with a thorough knowledge of the particular procedure to be performed. Appropriate facilities should be available for coping with any complication of the procedure, as well as for emergency treatment of severe reactions to the contrast agent itself. After parenteral administration of a radiopaque agent, competent personnel and emergency facilities should be available for at least 30 to 60 minutes since severe delayed reactions have occurred (see ADVERSE REACTIONS—General).

The possibility of a reaction, including serious, life-threatening, fatal, anaphylactic or cardiovascular reactions should always be considered (see ADVERSE REACTIONS). It is of utmost importance that a course of action be carefully planned in advance for immediate treatment of serious reactions, and that adequate and appropriate personnel be readily available in case of any reaction.

Preparatory dehydration for angiography and CT procedures is unnecessary and may be dangerous, contributing to acute renal failure in infants, young children, the elderly, patients with preexisting renal insufficiency, patients with advanced vascular disease, and diabetic patients. Dehydration in these patients seems to be enhanced by the osmotic diuretic action of urographic agents. Overnight fluid retention for urography may be undesirable and is considered unnecessary when using this relatively high (60%) concentration.

Although azotemia is not a contraindication, the medium should be used with great care in patients with advanced renal destruction associated with severe uremia. (See also EXCRETORY UROGRAPHY, precautions).

Acute renal failure has been reported in diabetic patients with diabetic nephropathy and in susceptible nondiabetic patients (often elderly with preexisting renal disease) following excretory urography. Therefore, careful consideration of the potential risks should be given before performing this radiographic procedure in these patients. (See also, EXCRETORY UROGRAPHY, precautions—Preparatory Dehydration.)

Immediately following surgery, excretory urography should be used with caution in renal transplant recipients.

The possibility of an idiosyncratic reaction in susceptible patients should always be considered (see ADVERSE REACTIONS—General). The susceptible population includes patients with a history of a previous reaction to a contrast medium, patients with a known sensitivity to iodine per se, and patients with a known clinical hypersensitivity: bronchial asthma, hay fever, and food allergies.

The occurrence of severe idiosyncratic reactions has prompted the use of several pretesting methods. However, pretesting cannot be relied upon to predict severe reactions and may itself be hazardous for the patient. It is suggested that a thorough medical history with emphasis on allergy and hypersensitivity, prior to injection of any contrast media, may be more accurate than pretesting in predicting potential adverse reactions.

A positive history of allergies or hypersensitivity does not arbitrarily contraindicate the use of a contrast agent, where a diagnostic procedure is thought essential, but caution should be exercised (see ADVERSE REACTIONS—General). Premedication with antihistamines or corticosteroids to avoid or minimize possible allergic reactions in such patients should be considered. Recent reports indicate that such pretreatment does not prevent serious life-threatening reactions, but may reduce both their incidence and severity.

Due to the transitory increase in the circulatory osmotic load, injections of urographic agents should be used with caution in patients with congestive heart failure. Such patients should be observed for several hours following the procedure to detect delayed hemodynamic disturbances.

General anesthesia may be indicated in the performance of some procedures in young or uncooperative children and in selected adult patients; however, a higher incidence of adverse reactions has been reported in these patients, and may be attributable to the inability of the patient to identify untoward symptoms, or to the hypotensive effect of anesthesia which can reduce cardiac output and increase the duration of exposure to the contrast agent.

Seizure activity is rare (about 0.01%) on intravenous injection of ionic contrast media. However, in the higher doses used for CT in patients with brain metastases the incidence can be much higher (1% to 10%). In these patients prophylactic use of a small parenteral dose of diazepam is suggested immediately before injection when extra high dose CT regimens are employed.

In addition to the general precautions already described, excretory urography, cholangiography, and other uses also have hazards associated with the particular techniques employed. (See INDIVIDUAL INDICATIONS AND USAGE section.)

Information for Patients

Patients receiving injectable radiopaque diagnostic agents should be instructed to:

1. Inform the physician if they are pregnant (see CLINICAL PHARMACOLOGY).
2. Inform the physician if they are diabetic or if they have multiple myeloma, pheochromocytoma, homozygous sickle cell disease or known thyroid disorder (see WARNINGS—General).
3. Inform the physician if they are allergic to any drugs, food, or if they have had any reactions to previous injections of dyes used for x-ray procedures (see PRECAUTIONS—General).
4. Inform the physician about any other medications they are currently taking, including nonprescription drugs, before they are administered this drug.

Drug Interactions

Renal toxicity has been reported in a few patients with liver dysfunction who were given oral cholecystographic agents followed by urographic agents. Administration of intravascular urographic agents should therefore be postponed in any patient with a known or suspected hepatic or biliary disorder who has recently received a cholecystographic contrast agent.

Addition of an inotropic agent to contrast agents may produce a paradoxical depressant response which can be deleterious to the ischemic myocardium.

Diphenhydramine hydrochloride may cause precipitation when mixed in the same syringe with HYPAQUE meglumine 60%.

Under certain circumstances (pH, temperature, concentrations, time), diatrizoate solutions are incompatible with promethazine hydrochloride, diphenhydramine hydrochloride, brompheniramine maleate, or papaverine hydrochloride solutions.

Do not prefill plastic syringes with HYPAQUE meglumine 60% for prolonged periods (ie, for several hours or longer) before use.

Drug/Laboratory Test Interactions

If any of these studies, which might be affected by contrast media are indicated, it is recommended that they be performed prior to administration of the contrast medium or two or more days afterwards.

Diatrizoate salts interfere with several laboratory urine and blood tests.

Blood Tests

Coagulation: Diatrizoate salts significantly inhibit all stages of coagulation. The fibrinogen concentration, Factors V, VII, and VIII are decreased. Prothrombin time and thromboplastin time are increased.

Platelet aggregation: High levels of plasma diatrizoates inhibit platelet aggregation.

Serum calcium: Diatrizoate salts may decrease serum calcium levels. However, this depletion of serum calcium may also be the result of the addition of chelating agents (edetate disodium) in the preparation of certain contrast media.

Red cell counts: Transitory decreases in red cell counts. Technetium-99m—RBC labeling interference.

Leukocyte counts: Decrease.

Urea nitrogen (BUN): Transitory increase (see CLINICAL PHARMACOLOGY).

Serum creatinine: Transitory increase.

Urine Test

Contrast media which are excreted in the urine, may interfere with some laboratory determinations eg, proteinuria, specific gravity, osmolality, or bacterial cultures.

Thyroid Function Test

Protein-bound iodine (PBI) and total serum organic iodine: Transient increase of both tests following urography have been noticed. The results of PBI and radioactive iodine uptake studies which depend on iodine estimations will not accurately reflect thyroid function for up to 16 days following administration of iodinated urographic media. However, thyroid function tests not depending on iodine estimations, eg, T3 resin uptake or free thyroxine assays are not affected.

Carcinogenesis, Mutagenesis, Impairment of Fertility

Long-term studies in animals have not been performed in order to evaluate carcinogenic potential, mutagenesis, or whether HYPAQUE meglumine 60 percent can affect fertility in males or females.

Pregnancy Category C

Animal reproduction studies have not been conducted with HYPAQUE meglumine 60 percent. It is also not known whether HYPAQUE meglumine 60 percent can cause fetal harm when administered to a pregnant woman or can affect reproduction capacity. HYPAQUE meglumine 60 percent should be given to a pregnant woman only if clearly needed. Doses up to 2500 mg/kg in rats, given IV daily, administered during gestation days 6 to 15 revealed no teratogenic abnormalities.

Labor and Delivery

It is not known whether use of these contrast agents during labor or delivery has immediate or delayed adverse effects on the fetus, prolongs the duration of labor or increases the likelihood that forceps delivery or other obstetrical intervention or resuscitation of the newborn will be necessary.

Nursing Mothers

Diatrizoate salts are excreted unchanged in human milk. Because of the potential adverse reactions, although it has not been established that serious adverse reactions occur in nursing infants, caution should be exercised when these intravascular contrast media are administered to a nursing woman.

Pediatric Use

Infants and small children should not have any fluid restriction prior to excretory urography or any other procedures (see PRECAUTIONS—General). Guidelines for pediatric dosages are presented in DOSAGE AND ADMINISTRATION–General.

ADVERSE REACTIONS—General

Approximately 95 percent of adverse reactions accompanying the intravascular use of diatrizoate salts are of mild to moderate severity. However, life-threatening reactions and fatalities, mostly of cardiovascular origin, have occurred.

Adverse reactions to injectable contrast media fall into two categories: chemotoxic reactions and idiosyncratic reactions.

Chemotoxic reactions result from the physicochemical properties of the contrast media, the dose, and the speed of injection. All hemodynamic disturbances and injuries to organs or vessels perfused by the contrast medium are included in this category.

Idiosyncratic reactions include all other reactions. They occur more frequently in patients 20 to 40 years old. Idiosyncratic reactions may or may not be dependent on the amount of dose injected, the speed of injection, the mode of injection, and the radiographic procedure. Idiosyncratic reactions are subdivided into minor, intermediate, and severe. The minor reactions are self-limited and of short duration; the severe reactions are life-threatening and treatment is urgent and mandatory.

The reported incidence of adverse reactions to contrast media in patients with a history of allergy are twice that of the general population. Patients with a history of previous reactions to a contrast medium are three times more susceptible than other patients. However, sensitivity to contrast media does not appear to increase with repeated examinations.

Most adverse reactions to injectable contrast media appear within one to three minutes after the start of injection, but delayed reactions may occur.

Adverse reactions are grouped by organ system and listed below by decreasing order of occurrence and with an approximate incidence of occurrence. Significantly more severe reactions are listed before the other reactions regardless of frequency.

Greater Than 1 in 100 Patients

Body as a Whole: Reported incidences of death range from 6.6 per 1 million (0.00066 percent) to 1 in 10,000 patients (0.01 percent). Most deaths occur during injection or 5 to 10 minutes later, the main feature being cardiac arrest with cardiovascular disease as the main aggravating factor.

Isolated reports of hypotensive collapse and shock following urography are found in the literature. The incidence of shock is estimated to occur in 1 out of 20,000 (0.005 percent) patients.

Cardiovascular System: The most frequent adverse reaction to diatrizoate salts is vasodilation (feeling of warmth). The estimated incidence is 49 percent.

Digestive System: Nausea 6 percent, vomiting 3 percent.

Nervous System: Paresthesia 6 percent, dizziness 5 percent.

Respiratory System: Rhinitis 1 percent, increased cough 2 percent.

Skin and Appendages: Urticaria 1 percent.

Pain at the injection site is estimated to occur in about 12 percent of the patients undergoing urography. Pain is usually due to extravasation.

Painful hot erythematous swelling above the venipuncture site was estimated to occur in more than one percent of the patients undergoing phlebography.

Special Senses: Perversion of taste 11 percent.

Urogenital System: Osmotic nephrosis of the proximal tubular cells is estimated to occur in 23 percent of patients following excretory urography.

Less Than 1 in 100 Patients

Other infrequently reported reactions without accompanying incidence rates are listed below, grouped by organ system.

Body as a Whole: Malaria relapse, uremia, high creatinine and BUN (see PRECAUTIONS—General Drug/Laboratory Test Interactions), thrombocytopenia, leukopenia and anemia.

Cardiovascular System: Cerebral hematomas, hemodynamic disturbances, sinus bradycardia, transient electrocardiographic abnormalities, ventricular fibrillation, petechiae, chest pain, cardiac arrest, tachycardia, and cardiorespiratory arrest.

Digestive System: Severe unilateral or bilateral swelling of the parotid and submaxillary glands.

Nervous System: Convulsions, paralysis, coma, speech impairment and severe confusion (see PRECAUTIONS—General).

Respiratory System: Asthma, dyspnea, laryngeal edema, pulmonary edema, bronchospasm, pulmonary embolus and respiratory arrest.

Skin and Appendages: Extravasation necrosis, urticaria with or without pruritus, mucocutaneous edema, and angioneurotic edema.

Special Senses: Bilateral ocular irritation, lacrimation, itching, conjunctival chemosis, infection, conjunctivitis and unilateral blindness.

Urogenital: Renal failure, pain.

OVERDOSAGE

At dosage levels of 1 mL/lb, the incidence of unpleasant side effects increases. At total dosage of 2 mL/lb, administered over a short period of time (eg, 30 minutes), clinical signs of systemic intolerance appear (mostly related to hyperosmolar effects) and are manifest as tremors, irritability, and tachycardia. Above these maximal tolerated dosage levels in otherwise healthy adults, an increasing incidence and severity of dyspnea and pulmonary edema should be expected.

Four cases of overdosage in infants, during urography, are reported. Three of the infants died within 19 hours of the injection. The overdose ranged from slightly above the recommended pediatric dosage to a dose exceeding 19 g/kg. The symptoms of overdosage appeared between 10 minutes to several hours after injection of the contrast medium. Adverse effects were life-threatening, affecting mainly the pulmonary and cardiovascular systems. The symptoms included: cyanosis, bradycardia, acidosis, pulmonary hemorrhage, convulsions, coma, and cardiac arrest. All infants showed a poor visualization of the kidneys and a diffuse opacification of all the tissues and vasculature. Autopsy findings showed acute pulmonary damage and/or edema of subcutaneous tissues. Treatment of an overdose of injectable radiopaque contrast media is directed toward the support of all vital functions, and prompt institution of symptomatic therapy.

The acute intravenous LD50 of diatrizoate meglumine in mice is equivalent in iodine content of 5.3 gI/kg to 8.0 gI/kg and seem to be directly proportional to the rate of injection.

Diatrizoate meglumine is dialyzable.

DOSAGE AND ADMINISTRATION—General

Preparation of the patient will vary with preference of the radiologist and the type of radiological procedure performed. Specific radiographic procedures used will depend on the state of the patient and the diagnostic indications. Individual dose should be tailored according to age, body size, and indication for examination. (See INDIVIDUAL INDICATIONS AND USAGE section for specific Dosage and Administration.)

Solutions of radiopaque diagnostic agents for intravascular use should be at body temperature when injected and may need to be warmed before use. In the event that crystallization occurs, the solution may be clarified by placing the vial in a water bath at 40°C to 50°C and shaking it gently for two to three minutes or until the solids redissolve. If the particles still persist, do not use this vial but discard it. The solution should be protected from light and any unused portion remaining in the container should be discarded.

Dilution and withdrawal of the contrast agents should be accomplished under aseptic conditions with sterile syringes.

Parenteral drug products should be inspected visually for particulate matter and discoloration prior to administration. Avoid contaminating catheters, syringes, needles, and contrast media with glove powder or cotton fibers.

Pediatric Dosage

Pediatric doses of injectable radiopaque diagnostic agents are generally determined on a weight basis and should be calculated for each patient individually. (See INDIVIDUAL INDICATIONS AND USAGE section.)

Drug Incompatibilities

Diatrizoate salts are incompatible in vitro with some antihistamines and many other drugs. It is believed that one of the chief causes of in vitro incompatibility is an alteration of pH. Turbidity of solutions of intravascular contrast medium occurs between pH 2.5 and 4.1. Another cause is chemical interaction; therefore, other pharmaceuticals should not be mixed with contrast agents in the same syringe.

INDIVIDUAL INDICATIONS AND USAGE

THE FOLLOWING SECTIONS FOR INDIVIDUAL INDICATIONS AND USAGE CONTAIN CONTRAINDICATIONS, WARNINGS, PRECAUTIONS, ADVERSE REACTIONS, AND DOSAGE AND ADMINISTRATION SECTIONS RELATED TO THE SPECIFIC PROCEDURES. HOWEVER, IT SHOULD BE UNDERSTOOD THAT THE INFORMATION IN THE GENERAL SECTIONS IS ALSO LIKELY TO APPLY TO ALL OF THESE SPECIFIC USES.

Hydration—With the possible exception of urography, patients should be fully hydrated prior to the following procedures.

EXCRETORY UROGRAPHY

Diatrizoate salts are used in small, medium, and large dose urography (see Dosage and Administration—EXCRETORY UROGRAPHY). Visualization of the urinary tract can be achieved by either direct intravenous injection, intravenous drip infusion, or sometimes by intramuscular or subcutaneous injections, or incidentally following intra-arterial procedure. Visualization of the urinary tract is delayed in infants less than 1 month old, and in patients with urinary tract obstruction (see CLINICAL PHARMACOLOGY).

Contraindication

Urography is contraindicated in patients with anuria.

Precautions

See PRECAUTIONS—General. Some clinicians consider multiple myeloma a contraindication to excretory urography because of the great possibility of producing transient to fatal renal failure. Others believe that the risk of causing anuria is definite but small. If excretory urography is performed in the presence of multiple myeloma, dehydration should be avoided since it favors protein precipitation in renal tubules.

Although azotemia is not considered a contraindication, care is required in patients with advanced renal failure. The usual preparatory dehydration should be omitted, and urinary output should be observed for one to two days in these patients. Adequate visualization may be difficult or impossible to attain in patients with severely impaired renal and/or hepatic function. Use with extreme caution in patients with concomitant hepatorenal disease.

Because of the possibility of temporary suppression of urine, it is wise to allow an interval of at least 48 hours before excretory urography is repeated in patients with unilateral or bilateral reduction of normal renal function. Inadvertent retrograde cystourethrography can cause malignant hyperthermia, disseminated intravascular coagulation and fatality.

Preparatory Dehydration

Preparatory dehydration is dangerous in infants, young children, the elderly, and azotemic patients (especially those with polyuria, oliguria, diabetes, advanced vascular disease, or preexisting dehydration). The undesirable dehydration in these patients may be accentuated by the osmotic diuretic action of the medium.

Dehydration may improve image quality in patients with adequate renal function particularly if a low dose is used. Dehydration, however, will not improve contrast quality in patients with substantial renal insufficiencies and will increase risk of contrast induced renal damage. Dehydration in these patients is therefore contraindicated.

Adverse Reactions

See ADVERSE REACTIONS—General.

Dosage and Administration

Intravenous Dosage

Adults: A dose of 30 mL to 60 mL produces excellent shadows in the majority of adults subjected to partial dehydration and effective purgation. In persons of slight build, 20 mL produces adequate shadows. For best results and minimal reactions, the total 30 mL to 60 mL should be injected in one to three minutes and compression may be used. A small intravenous test dose may be administered as a possible aid in determining sensitivity to the medium. (See PRECAUTIONS—General.)

Children: The suggested dosage for children up to 12 years old is presented in the table below. Children older than 12 years may be given an adult dose.

Pediatric Dosage for Excretory Urography
Age | Body Weight | Dosage
Under 2 years | up to 10 lb | 5 mL to 10 mL
 | 10 to 30 lb | 10 mL to 15 mL
2 to 12 years | 30 to 60 lb | 15 mL to 30 mL
 | over 60 lb | 30 mL

Preliminary Preparation of Patient

Although clear shadows are often seen in patients who have had no preliminary preparation for urography, the largest percentage of satisfactory films is obtained in patients who abstain from fluids for 12 to 15 hours before the intravenous injection so that partial dehydration results. (See PRECAUTIONS—General concerning dehydration.) Unless contraindicated, a laxative may be taken at bedtime to eliminate gas from the intestine.

Roentgenographic Technique

A preliminary scout film may be obtained before the intravenous injection. Excellent shadows can often be obtained immediately after administration of the radiopaque medium (within a five-minute period). If preliminary preparation has been carried out, the urinary organs are usually best visualized on films exposed 5, 10, or 15 minutes after intravenous injection. If a film of the bladder is required, it is generally taken 25 or 35 minutes after injection.

In patients with impaired renal function, the best shadows may not be obtainable until later (30 minutes or more) because of delayed excretion, and additional film may have to be exposed.

Most urologists and roentgenologists believe that compression immediately above the symphysis (obtained by application of a small hollow rubber ball about the size of a grapefruit or by the rolled bed sheet technique) assures adequate filling of the pelves and ureters, and hence is of great value. Although compression undoubtedly improves the urogram, it also seems to increase the possibility of pyelorenal backflow or reflux by raising the pressure within the urinary tract.

ANGIOGRAPHY

Precautions

Since serious neurologic complications, including quadriplegia, have occasionally been reported following spinal arteriography or selective injection of arterial trunks providing spinal artery branches (usually the thyrocervical, costocervical, subclavian, vertebral, bronchial, intercostal), great care is necessary to avoid entry of a large concentrated bolus of the medium. Thus, a "pilot" dose may establish correct position of the catheter tip. The concentration of the medium should not be over 60 percent. The carefully individualized dose is usually under 5 mL but preferably 3 mL to 4 mL and the number of repeat injections held to a minimum with appropriate intervals between injections. Pain or muscle spasm during the injection may require reevaluation of the procedure.

Angiography should be avoided whenever possible in patients with homocystinuria, because of the risk of inducing thrombosis and embolism.

CEREBRAL ANGIOGRAPHY

Indication

HYPAQUE meglumine 60 percent may be administered for visualization of the cerebral vessels. In as much as cerebral angiography is a highly specialized procedure requiring the use of special techniques, it is recommended that HYPAQUE meglumine 60 percent be used for this purpose only by persons skilled and experienced in carrying out the procedure.

Contraindication

Carotid angiography during the progressive period of a stroke should be avoided, particularly on the left side because of the increased risk of cerebral complications.

Precautions

See PRECAUTIONS—General. Patients in whom cerebral angiography is to be performed should be selected with care.

Although cerebral angiography has been considered contraindicated in patients who have recently experienced cerebral embolism or thrombosis (stroke syndrome), many experts now believe that the diagnostic value of the procedure, when employed early as an aid in locating lesions amenable to operation, outweighs any added risk to the patient. Furthermore, a small number of postangiographic fatalities have been reported, including progressive thrombosis already clinically evident before angiography, in which the procedure did not appear to play any direct role. Patients with severe cerebrovascular disease should be examined primarily by indirect methods of angiography.

In cerebral angiography, every precaution must be taken to prevent untoward reactions. Reactions may vary directly with the concentration of the substance, the amount used, the speed and frequency of injections, and the interval between injections.

In subarachnoid hemorrhage, angiography is expected to be hazardous. In migraine, the procedure can be hazardous because of ischemic complications, particularly if performed during or soon after an attack.

Adverse Reactions

See ADVERSE REACTIONS—General. With any contrast medium introduced into the cerebral vasculature, neurologic complications, including neuromuscular disorders, seizures, loss of consciousness, hemiplegia, unilateral dysesthesias, visual field defect, language disorders (aphasia), amnesia, and respiratory difficulties may occur, particularly when the extent of the intrinsic lesion is unknown. Such untoward reactions are for the most part temporary, although permanent visual field defects have been reported. Some investigators who are experienced in angiographic procedure emphasize the fact that they tend to occur after repeated injections or higher doses of the contrast medium. Other clinicians find that they occur most frequently in elderly patients. Inasmuch as the procedure itself is attended by technical difficulties regardless of the risk the patient presents (eg, mechanical catheter obstruction of the vertebral artery can cause transient blindness), the more experienced the radiologic team, the fewer the complications of any degree that are apt to arise.

Amaurosis can occur following carotid or especially selective vertebral arteriography. It is almost always transitory (4 to 48 hours).

Dosage and Administration

A dose of 8 mL to 12 mL injected at a rate not exceeding the normal flow in the carotid artery (about 5 mL per second) is suggested. The dose may be repeated as indicated; however, an increased risk attends each repeat injection. Children require a smaller dose in proportion to weight. Light anesthesia may be required in these procedures.

PERIPHERAL ARTERIOGRAPHY AND VENOGRAPHY

Indications

HYPAQUE meglumine 60 percent may be administered for peripheral arteriography and for venography.

Precautions

See PRECAUTIONS—General. Extreme caution is advised in considering peripheral arteriography in patients suspected of having thromboangiitis obliterans (Buergers disease) since any procedure (even insertion of a needle or catheter) may induce a severe arterial or venous spasm. Caution is also advisable in patients with severe ischemia associated with ascending infection.

Adverse Reactions

See ADVERSE REACTIONS—General. Soreness in extremities has also been reported.

Adverse reactions observed during peripheral arteriography may sometimes be due to arterial trauma during the procedure (ie, insertion of needle or catheter, subintimal injection, perforation) as well as to the hypertonicity or effect of the medium. Reported adverse reactions include transient arterial spasm, extravasation, hemorrhage, hematoma formation with tamponade, injury to nerves in close proximity to artery, thrombosis, dissecting aneurysm, arteriovenous fistula (eg, with accidental perforation of femoral artery and vein during the needing), and transient leg pain from contraction of calf muscles in femoral arteriography. Transient hypotension has been reported after intra-arterial (brachial) injection of the medium. Also, brachial plexus injury has been reported with axillary artery injections.

During venography in the presence of venous stasis, inflammatory changes and thrombosis may occur. Thrombosis is rare if the vein is irrigated following the injection.

Dosage and Administration

Diagnostic arteriograms may be obtained with 20 mL to 40 mL of HYPAQUE meglumine 60 percent introduced into the larger peripheral arteries by percutaneous or operative methods. Visualization of veins in the extremities may be accomplished with 10 mL to 20 mL.

DIRECT CHOLANGIOGRAPHY

Contraindication

Percutaneous transhepatic cholangiography is contraindicated in patients with coagulation defects and prolonged prothrombin times until normal, or near normal, coagulation is achieved (eg, with vitamin K).

Precautions

In the presence of acute pancreatitis, direct cholangiography, if necessary, should be employed with caution, injecting no more than 5 mL to 10 mL without undue pressure.

Percutaneous transhepatic cholangiography should only be attempted when compatible blood for potential transfusions is in readiness and emergency surgical measures are available. The patient should be carefully monitored for at least 24 hours to insure prompt detection of bile leakage and hemorrhage. Cholespastic premedication, as with morphine, should be avoided. Respiratory movements should be controlled during introduction of the needle.

Adverse Reactions

Adverse reactions may often be attributed to injection pressure or excessive volume of the medium, resulting in overdistention. Such pressure may produce a sensation of epigastric fullness, followed by moderate pain in the back or right upper abdominal quadrant, which will subside when injection is stopped.

Hepatobiliary reflux of the medium may cause a pancholangitis or hepatitis which is usually transitory. Retrograde spread of the infection may produce liver abscess or septicemia. Pancreatic duct reflux may cause a transitory increase in serum amylase for a period of 6 to 18 hours without ill effects. Rarely it may cause pancreatitis.

In percutaneous transhepatic cholangiography, some discomfort is common, but severe pain is unusual. Complications of the procedure are often serious and have been reported in four to six percent of patients. These reactions have included bile leakage and peritonitis, which are more likely to occur in patients with obstructions that cause unrelieved high biliary pressure. Bleeding (sometimes massive with exsanguination) may occur, especially in patients with clotting abnormalities. Blood-bile fistula, manifested by an early urogram (within 2 minutes) has been reported. Hypotension with fever and chills, as manifestations of septicemia, have occurred. Tension pneumothorax, cholangitis, and bacteremia have been reported.

Dosage and Administration

The solution should be warmed to body temperature before administration. The injection is made slowly without undue pressure, taking great care to avoid introducing bubbles.

Operative—If no resistance is encountered, from 10 mL to 15 mL (sometimes up to 25 mL) of a 30 to 60 percent solution is injected or instilled into the cystic duct or common bile duct, as indicated. In patients with obstructive jaundice, 40 mL to 50 mL of the medium may be injected indirectly into the gallbladder after aspiration of its contents.

Postexploratory or completion T tube cholangiography may also be performed after exploration of the common bile duct.

Postoperative—Delayed cholangiograms are usually made from the fifth to the tenth postoperative day prior to removal of the T tube.

Percutaneous transhepatic cholangiography is recommended for carefully selected patients for the differential diagnosis of jaundice due to extrahepatic biliary obstruction or parenchymal disease. The procedure is only employed where oral or intravenous cholangiography and other procedures have failed to provide the necessary information. In obstructive cases, percutaneous transhepatic cholangiography is used to determine the cause and site of the obstruction to help plan surgery. The technique may also be of value in avoiding laparotomy in poor risk jaundice patients since failure to enter a duct suggests hepatocellular disease. Careful attention to technique is essential for the success and safety of the procedure. The procedure is usually performed under local anesthesia following analgesic premedication (eg, 100 mg meperidine intramuscularly).

As the needle is advanced or withdrawn, a bile duct may be located by frequent aspiration for bile or mucus into a syringe filled with normal saline. As much bile as possible is aspirated. The usual dose of HYPAQUE meglumine 60 percent is 20 mL to 40 mL but the range can be from 10 mL to 60 mL depending on degree of biliary dilatation present. The injection may be repeated for exposures in different planes. If a duct is not readily located by aspiration, entry may be established by the injection of successive small doses of 1 mL or 2 mL of the medium under x-ray observation as the needle is withdrawn. If a duct is not located after three or four attempts, the procedure should be abandoned. Inability to enter a duct strongly suggests hepatocellular disease.

SPLENOPORTOGRAPHY

Indication

Splenoportography is usually performed under mild preoperative sedation and under local anesthesia.

Contraindications

Splenoportography should not be performed on any patient for whom splenectomy is contraindicated, since complications of the procedure at times make splenectomy necessary. Other contraindications include prolonged prothrombin time or other coagulation defects, significant thrombocytopenia, and any condition which may increase the possibility of rupture of the spleen.

Precautions

Prior gastrointestinal x-ray examination should include particular attention to the lower esophageal area. A hematologic survey, including prothrombin time and platelet count, should be performed. To minimize risk of bleeding, manipulation during or after entry of the needle should be avoided. Caution is advised in patients whose spleen has recently become tender and palpable.

Following splenoportography, the patient should lie on his left side for several hours and should be closely observed for 24 hours for signs of internal bleeding.

Adverse Reactions

Internal bleeding is the most common serious complication of splenoportography. Although leakage of up to 300 mL of blood is apparently not uncommon, sometimes blood transfusions and, rarely, splenectomy, may be required to control hemorrhage. Peritoneal extravasation may cause transient diaphragmatic irritation or mild to moderate transient pain which may sometimes be referred to the shoulder, the periumbilical region, or other areas. Because of the proximity of the pleural cavity, accidental pneumothorax has been known to occur. Inadvertent injection of the medium into other nearby structures is not likely to cause untoward consequences.

Dosage and Administration

A preliminary small "pilot" dose is injected to confirm splenic entry, followed usually by rapid injection of 20 mL to 25 mL of HYPAQUE meglumine 60 percent. Rapid serial exposures are started with the injection of the dose and continued until contrast is observed in the entire portal system.

ARTHROGRAPHY

Indications

Arthrography may be helpful in the diagnosis of posttraumatic or degenerative joint diseases, synovial rupture, the visualization of communicating bursae or cysts, and in meniscography. However, the technique is of little value unless the arthrograms are interpreted by well-trained personnel.

Contraindication

Arthrography is contraindicated when there is infection in or near the joint.

Precautions

See PRECAUTIONS—General. A strict, aseptic technique is required to avoid introducing infection.

Adverse Reactions

See ADVERSE REACTIONS—General. Injection of HYPAQUE meglumine 60 percent into the joint usually causes immediate but transient discomfort. However, delayed, severe, or persistent pain may occur occasionally. Severe pain often results from undue use of pressure or the injection of large volumes. Joint swelling after injection is rare. Effusion, occasionally requiring aspiration, can occur in patients with rheumatoid arthritis.

Dosage and Administration

The procedure is usually performed with analgesic premedication and under local anesthesia. The amount of HYPAQUE meglumine 60 percent injected depends solely on the capacity of the joint. The damaged joint may require doses greatly exceeding those for normal joints. As much fluid as possible should first be aspirated from the joint; then, the medium should be injected gently to avoid overdistention of the joint capsule. Passive manipulation is sometimes used to disperse the medium in the joint. Sometimes, a 1 mL or 2 mL test dose is injected; immediate pain may indicate extravasation or extracapsular injection which, if confirmed by x-ray, requires relocation of the needle.

A single injection is usually adequate for multiple exposures. Contrast is good during the first 10 minutes after injection, adequate at 10 to 15 minutes, and begins to fade at 15 to 25 minutes.

The following approximate volumes have been used in normal adult joints:

Knee, shoulder, hip—5 mL to 15 mL
Temporomandibular—0.5 mL
Other—1 mL to 4 mL

"Double contrast arthrography," using a mixture of the medium and air or a dilution of HYPAQUE meglumine 60 percent to a 30 percent concentration, has been employed.

DISCOGRAPHY

Indications

Cervical discography is a more hazardous procedure than lumbar discography, and the interpretation of the cervical discograms is more difficult.

The injected medium gradually diffuses throughout the disc and is absorbed rapidly. In a normal disc, good contrast is evident for 10 to 15 minutes. In a ruptured disc, the medium is absorbed more rapidly. Aspiration of the medium on completion of discography is considered unnecessary.

Contraindication

Discography is contraindicated when there is infection or open injury near the region to be examined.

Warning

Inadvertent subarachnoid injection must be avoided since even the small dose of the medium used in discography might result in convulsions and death. The onset of signs of pain, cramps, or convulsions (requiring anesthesia) may occur within minutes to an hour.

Precautions

A strict, aseptic technique is required to avoid introducing infection. The examination should be postponed if local or systemic infection is present. In cervical discography, care should be taken to avoid contamination of the disc by inadvertent puncture of the esophagus. Laceration of the disc by use of a needle that has become barbed by forceful impingement on a vertebra, should be avoided. The patient should be cautioned not to move during introduction of the needle.

Adverse Reactions

In the normal disc, only minor discomfort will occur during injection. More discomfort will result if excessive pressure or volume is used. Pain is unusual and may indicate extravasation.

In the damaged disc, however, the injection can cause pain, sometimes severe, which mimics the symptoms. Transient backache or headache, as in lumbar puncture, often occurs. Extravasation from the disc into the lateral recesses and extradurally into the spinal canal or local soft tissue does not usually cause adverse effects.

During discography extreme care is advised to avoid inadvertent intrathecal injection since the injection of even small amounts of the contrast medium may cause convulsions, permanent sequelae, or fatality. Should the accident occur, the patient should be placed upright to confine the hyperbaric solution to a low level, anesthesia may be required to control convulsions, and if there is evidence of a large dose having been administered, a careful cerebrospinal fluid exchange-washout should be considered.

Dosage and Administration

Discography is usually performed with parenteral analgesia or sedation, and under local anesthesia. To minimize disc and tissue trauma, a two-needle technique is usually employed. An 18 to 20 gauge needle is used to penetrate to the disc and then a very fine (25 or 26 gauge) lumbar puncture-type needle is inserted through the needle to penetrate the disc.

Because of the resistance encountered, it is difficult to inject more than 0.2 mL to 0.3 mL of HYPAQUE meglumine 60 percent into a normal disc. Occasionally, however, a cervical disc can accept up to 0.5 mL and a lumbar disc, 1 mL (rarely, 2 mL) before resistance is encountered. Mild discomfort with little or no frank pain may indicate a normal disc.

In ruptured and some abnormal discs, 1 mL to 2 mL or more can be introduced without resistance; and, particularly if only one disc has pathology, the patient usually experiences pain, sometimes severe, with distribution characteristic of his symptoms. To minimize the amount of HYPAQUE extravasated, no more than 2 mL is injected in any one disc.

The procedure should be planned so that the duration of the discogram allows multiple exposures with a single dose. It has been recommended for diagnostic reasons that the procedure (injection and discogram) be performed on one disc at a time. Injection of a number of discs under suspicion, however, may be performed as part of one procedure.

CONTRAST ENHANCEMENT OF COMPUTED TOMOGRAPHIC HEAD IMAGING

Precautions

Metastatic Brain Lesions: Large doses of contrast media should be avoided in patients with suspected metastatic brain lesions. Intravenous administration of large doses to these patients is more likely to result in convulsions; however, these occurrences are rare. This has been attributed to tissue accumulation of the medium in the presence of blood brain barrier disruption caused by disease. Appropriate measures for seizure management should be immediately available.

Convulsion. (See PRECAUTIONS—General.)

Dosage and Administration

Bolus intravenous injection of 50 mL to 100 mL, or up to 150 mL by infusion. The rate of injection and the timing of scans will depend principally on the expected nature of the pathology. Dosage in children is proportional to adults, based on weight.

HOW SUPPLIED

Vials of 50 mL, rubber stoppered, box of 25 (NDC 0407-0746-04).

Vials of 100 mL, rubber stoppered, box of 10 (NDC 0407-0747-02).

Box of 10 calibrated 200 mL dilution bottles with hangers containing 150 mL HYPAQUE meglumine 60%; rubber stoppered (NDC 0407-0749-20).

Box of 10 calibrated 200 mL dilution bottles with hangers containing 200 mL HYPAQUE meglumine 60%; rubber stoppered (NDC 0407-0750-10).

Protect from light. Store at 15°C to 30°C (59° F to 86°F).

Distributed by Amersham Health Inc.
Princeton, NJ 08540

Printed in USA

Revised March 2002
HNC-8B